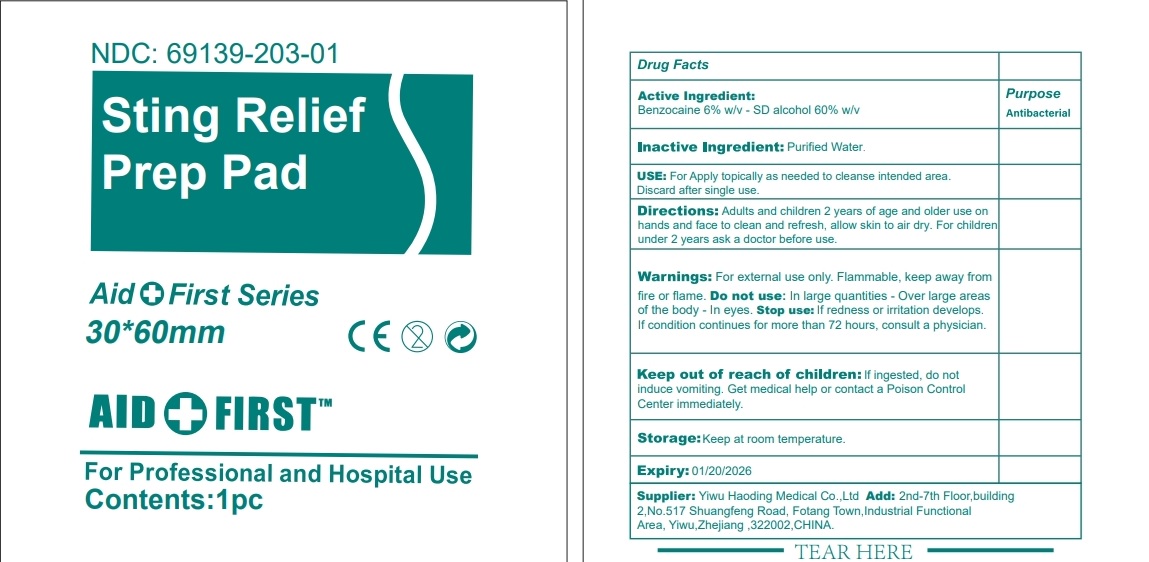 DRUG LABEL: aid and first sting relief prep pad
NDC: 69139-203 | Form: SWAB
Manufacturer: YIWU HAODING MEDICAL CO.,LTD
Category: otc | Type: HUMAN OTC DRUG LABEL
Date: 20240109

ACTIVE INGREDIENTS: BENZOCAINE 6 g/100 g; ISOPROPYL ALCOHOL 60 g/100 g
INACTIVE INGREDIENTS: WATER

Active ingredient

Benzocaine 6% w/v

SD alcohol 60% w/v

Purpose

Antibacterial

Uses

Apply topically as needed to cleanse intended area.

Discard after single use.

Warnings

For external use only.

Flammable, keep away for fire or flame.

Do not use

- In large quantities
- Over large areas of the body
- In eyes

Stop use and ask a doctor if conditions worsen or persist.

Stop use and ask a doctor if

- the conditions persist or worsen

Keep out of reach of children.

If swallowed, get medical help or contact a Poison Control Center right away.

Directions

Adults and children 2 years of age and older use on hands and face to clean and refresh, allow skin to air dry

For children under 2 years ask a doctor before use.

Tear open packet, unfold towelltte and use to clean desired skin area, discard towelltte appropriately after use.

Inactive ingredients

purified water